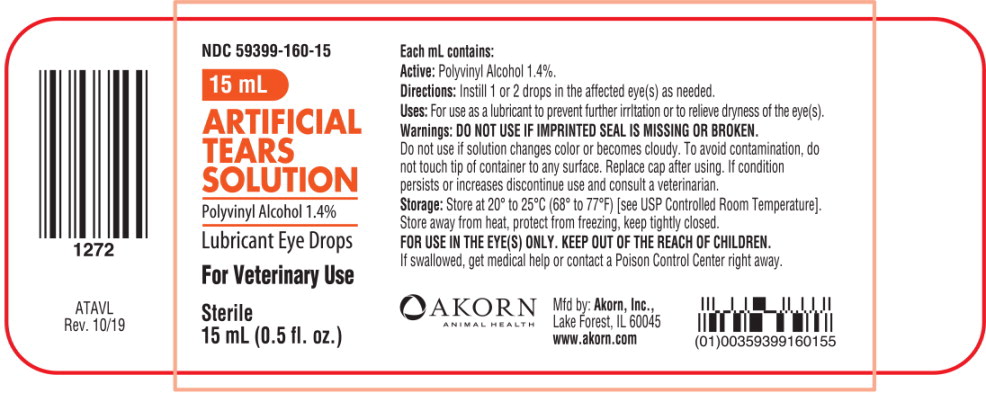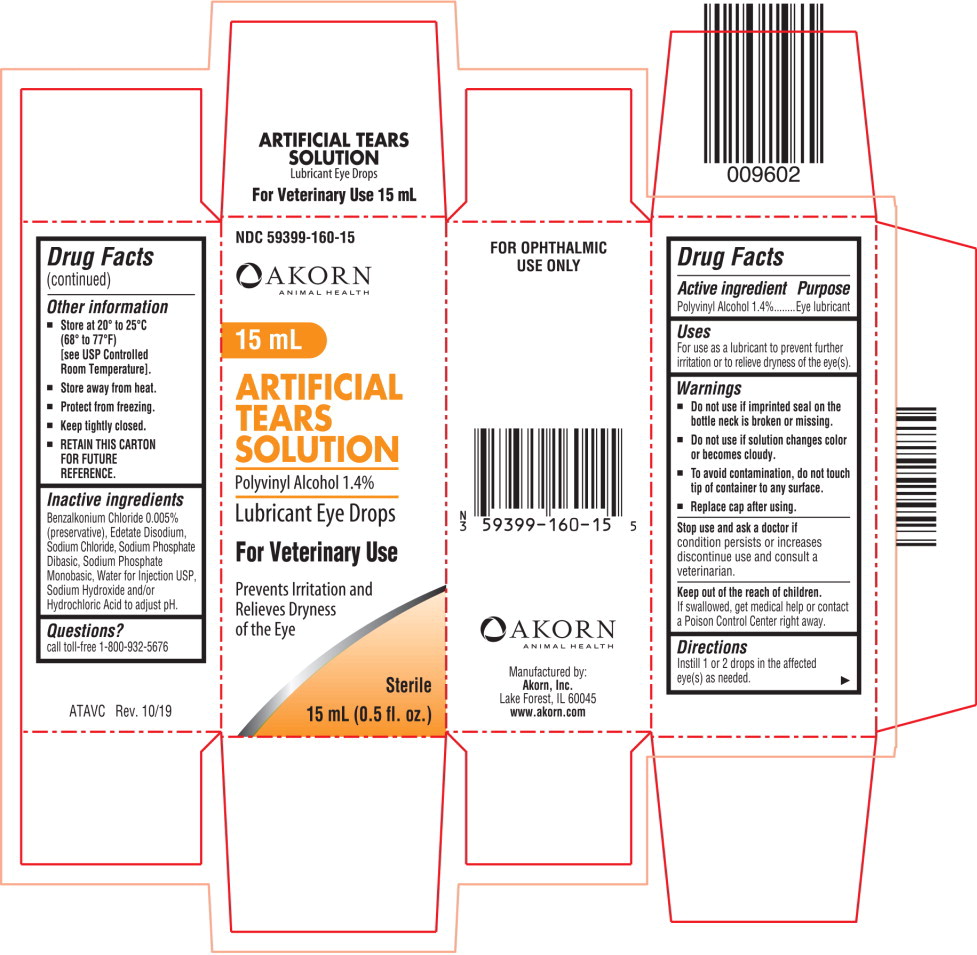 DRUG LABEL: Artificial Tears
NDC: 59399-160 | Form: SOLUTION/ DROPS
Manufacturer: Akorn
Category: animal | Type: OTC ANIMAL DRUG LABEL
Date: 20221103

ACTIVE INGREDIENTS: Polyvinyl Alcohol, Unspecified 14 mg/1 mL
INACTIVE INGREDIENTS: Benzalkonium Chloride; Edetate Disodium; Sodium Chloride; Sodium Phosphate, Dibasic, Anhydrous; Sodium Phosphate, Monobasic, Anhydrous; Water; Sodium Hydroxide; Hydrochloric Acid

Drug Facts

Active ingredient

Polyvinyl Alcohol 1.4%

Purpose

Eye lubricant

Uses

For use as a lubricant to prevent further irritation or to relieve dryness of the eye(s).

Warnings

- Do not use if imprinted seal on the bottle neck is broken or missing.
- Do not use if solution changes color or becomes cloudy.
- To avoid contamination, do not touch tip of container to any surface.
- Replace cap after using.

Stop use and ask a doctor if

condition persists or increases discontinue use and consult a veterinarian.

Keep out of the reach of children.

If swallowed, get medical help or contact a Poison Control Center right away.

Directions

Instill 1 or 2 drops in the affected eye(s) as needed.

Other information

- Store at 20° to 25°C (68° to 77°F)
  [see USP Controlled Room Temperature].
- Store away from heat.
- Protect from freezing.
- Keep tightly closed.
- RETAIN THIS CARTON FOR FUTURE REFERENCE.

Inactive ingredients

Benzalkonium Chloride 0.005% (preservative), Edetate Disodium, Sodium Chloride, Sodium Phosphate Dibasic, Sodium Phosphate Monobasic, Water for Injection USP, Sodium Hydroxide and/or Hydrochloric Acid to adjust pH.

Questions?

call toll-free 1-800-932-5676

Principal Display Panel Text for Container Label:

NDC 59399-160-15

15 mL

ARTIFICIAL

TEARS

SOLUTION

Polyvinyl Alcohol 1.4%

Lubricant Eye Drops

For Veterinary Use

Sterile

15 mL (0.5 fl. oz.)

Principal Display Panel Text for Carton Label:

NDC 59399-160-15

Akorn Animal Health Logo

15 mL

ARTIFICIAL

TEARS

SOLUTION

Polyvinyl Alcohol 1.4%

Lubricant Eye Drops

For Veterinary Use

Prevents Irritation and

Relieves Dryness

of the Eye

Sterile

15 mL (0.5 fl. oz.)